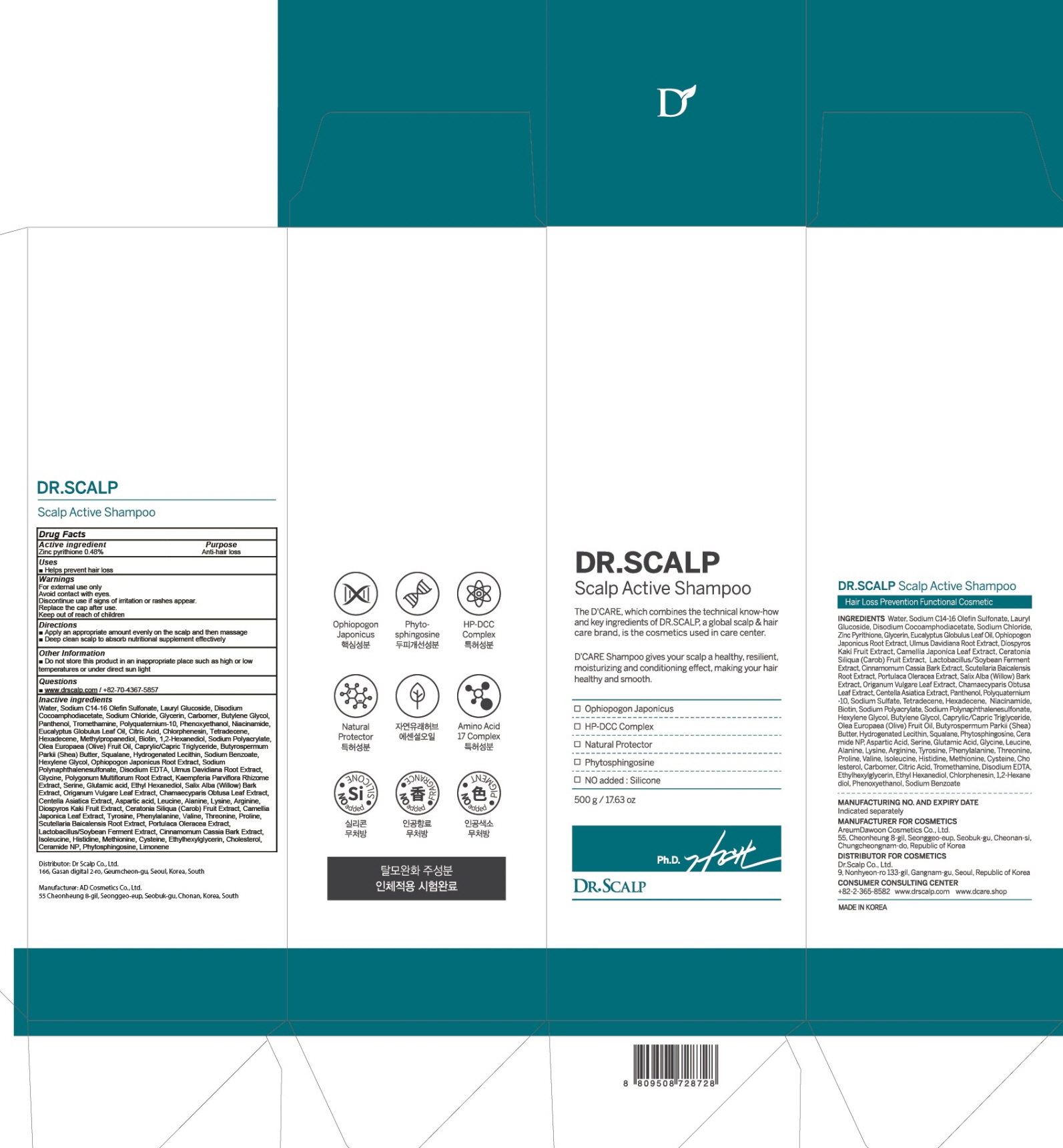 DRUG LABEL: DR. SCALP ACTIVE
NDC: 82343-010 | Form: SHAMPOO
Manufacturer: Dr Scalp Co., Ltd.
Category: otc | Type: HUMAN OTC DRUG LABEL
Date: 20211103

ACTIVE INGREDIENTS: PYRITHIONE ZINC 2.4 g/500 g
INACTIVE INGREDIENTS: Water; Sodium C14-16 Olefin Sulfonate; Lauryl Glucoside

ACTIVE INGREDIENT

Zinc pyrithione 0.48%

PURPOSE

Anti-hair loss

Uses

■ Helps prevent hair loss

WARNINGS

For external use only
Avoid contact with eyes.
Discontinue use if signs of irritation or rashes appear.
Replace the cap after use.
Keep out of reach of children

KEEP OUT OF REACH OF CHILDREN

Directions

■ Apply an appropriate amount evenly on the scalp and then massage
■ Deep clean scalp to absorb nutritional supplement effectively

Other Information

■ Do not store this product in an inappropriate place such as high or low temperatures or under direct sun light

Questions

■ www.drscalp.com / +82-70-4367-5857

INACTIVE INGREDIENTS

Water, Sodium C14-16 Olefin Sulfonate, Lauryl Glucoside, Disodium Cocoamphodiacetate, Sodium Chloride, Glycerin, Carbomer, Butylene Glycol,
Panthenol, Tromethamine, Polyquaternium-10, Phenoxyethanol, Niacinamide, Eucalyptus Globulus Leaf Oil, Citric Acid, Chlorphenesin, Tetradecene, Hexadecene, Methylpropanediol, Biotin, 1,2-Hexanediol, Sodium Polyacrylate, Olea Europaea (Olive) Fruit Oil, Caprylic/Capric Triglyceride, Butyrospermum Parkii (Shea) Butter, Squalane, Hydrogenated Lecithin, Sodium Benzoate, Hexylene Glycol, Ophiopogon Japonicus Root Extract, Sodium Polynaphthalenesulfonate, Disodium EDTA, Ulmus Davidiana Root Extract, Glycine, Polygonum Multiflorum Root Extract, Kaempferia Parviflora Rhizome Extract, Serine, Glutamic acid, Ethyl Hexanediol, Salix Alba (Willow) Bark Extract, Origanum Vulgare Leaf Extract, Chamaecyparis Obtusa Leaf Extract, Centella Asiatica Extract, Aspartic acid, Leucine, Alanine, Lysine, Arginine, Diospyros Kaki Fruit Extract, Ceratonia Siliqua (Carob) Fruit Extract, Camellia Japonica Leaf Extract, Tyrosine, Phenylalanine, Valine, Threonine, Proline, Scutellaria Baicalensis Root Extract, Portulaca Oleracea Extract, Lactobacillus/Soybean Ferment Extract, Cinnamomum Cassia Bark Extract, Isoleucine, Histidine, Methionine, Cysteine, Ethylhexylglycerin, Cholesterol, Ceramide NP, Phytosphingosine, Limonene